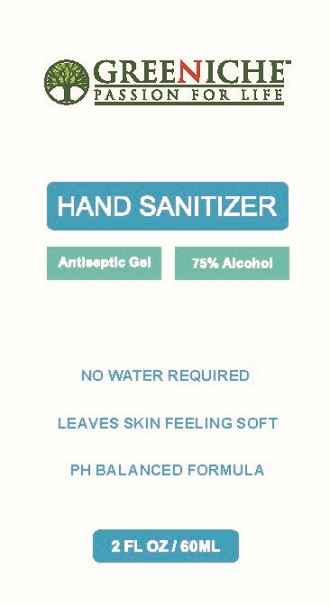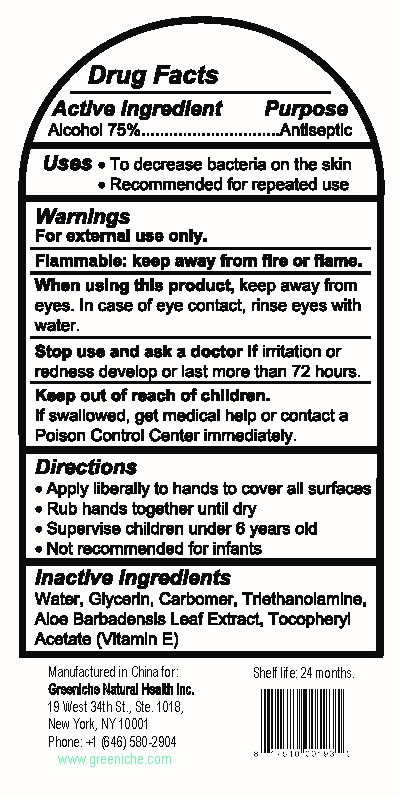 DRUG LABEL: Greeniche Hand Sanitizer
NDC: 80055-002 | Form: GEL
Manufacturer: Greeniche Natural Health Inc.
Category: otc | Type: HUMAN OTC DRUG LABEL
Date: 20200828

ACTIVE INGREDIENTS: ALCOHOL 75 mL/100 mL
INACTIVE INGREDIENTS: TROLAMINE; ALPHA-TOCOPHEROL ACETATE; GLYCERIN; WATER; CARBOMER 934; ALOE VERA LEAF

Greeniche Hand Sanitizer Gel with Aloe

Drug Facts

Active ingredient

Alcohol 75%

Purpose

Antiseptic

Uses

- to decrease bacteria on the skin.
- recommended for repeated use.

Warnings
For external use only.

Flammable. Keep away from fire and flame.

When using this product keep away from eyes. In case of contact, flush eyes thoroughly with water.

Stop use and ask a doctor if irritation or redness develop or persist for more than 72 hours.

Keep out of reach of children. If swallowed, get medical help or contact a Poison Control Center right away.

Directions

- Apply liberally to hands to cover all surfaces
- Rub hands together until dry.
- Supervise children under 6 years old
- Not recommended for infants

Inactive ingredients

Water, Glycerin, PEG-Glyceryl Cocoate, Carbomer, Triethanolamine

Manufactured in China for:
Greeniche Natural Health Inc.
19 West 34th St., Ste 1018

New York, NY 10001
Phone +1 (646) 580-2904
www.greeniche.com

PACKAGE LABEL

GREENICHE™

PASSION FOR LIFE

HAND SANITIZER

Antiseptic Gel

75% Alcohol

NO WATER REQUIRED

LEAVES SKIN FEELING SOFT

PH BALANCED PRODUCT

2 FL OZ / 60 ML